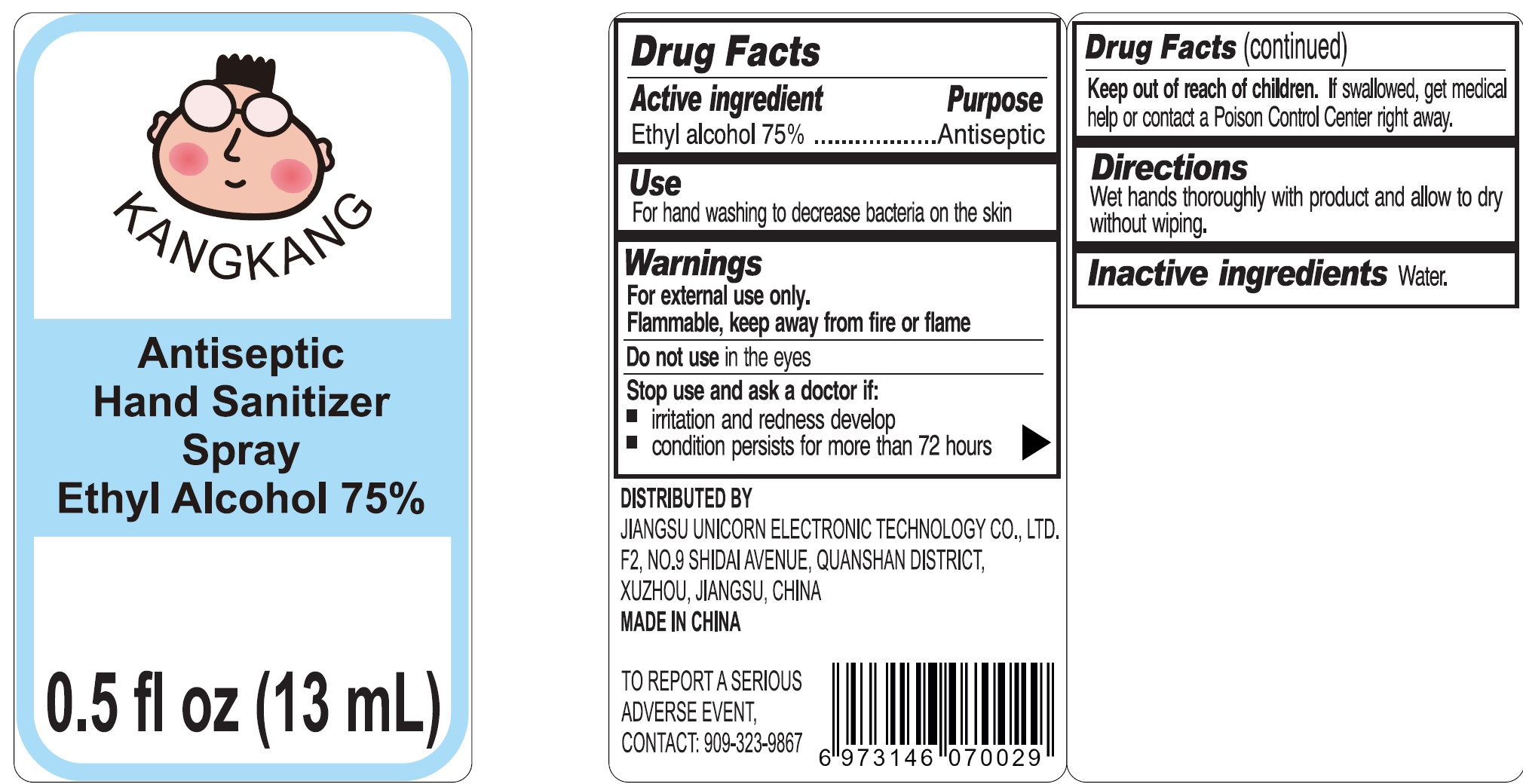 DRUG LABEL: KANGKANG Antiseptic Hand Sanitizer Ethyl Alcohol 75
NDC: 90074-000 | Form: LIQUID
Manufacturer: Jiangsu Unicorn Electronic Technology Co.,Ltd
Category: otc | Type: HUMAN OTC DRUG LABEL
Date: 20200928

ACTIVE INGREDIENTS: ALCOHOL 0.75 mL/1 mL
INACTIVE INGREDIENTS: WATER

KANGKANG Antiseptic Hand Sanitizer Spray Ethyl Alcohol 75%

Active ingredient

Ethyl alcohol 75%

Purpose

Antiseptic

Use

For hand washing to decrease bacteria on the skin

Warnings

For external use only.

Flammable, keep away from fire or flame

Do not use

in the eyes

Stop use and ask a doctor if:

- irritation and redness develop
- condition persists for more than 72 hours

Keep out of reach of children.

If swallowed, get medical help or contact a Poison Control Center right away.

Directions

Wet hands thoroughly with product and allow to dry without wiping.

Inactive ingredients

Water.